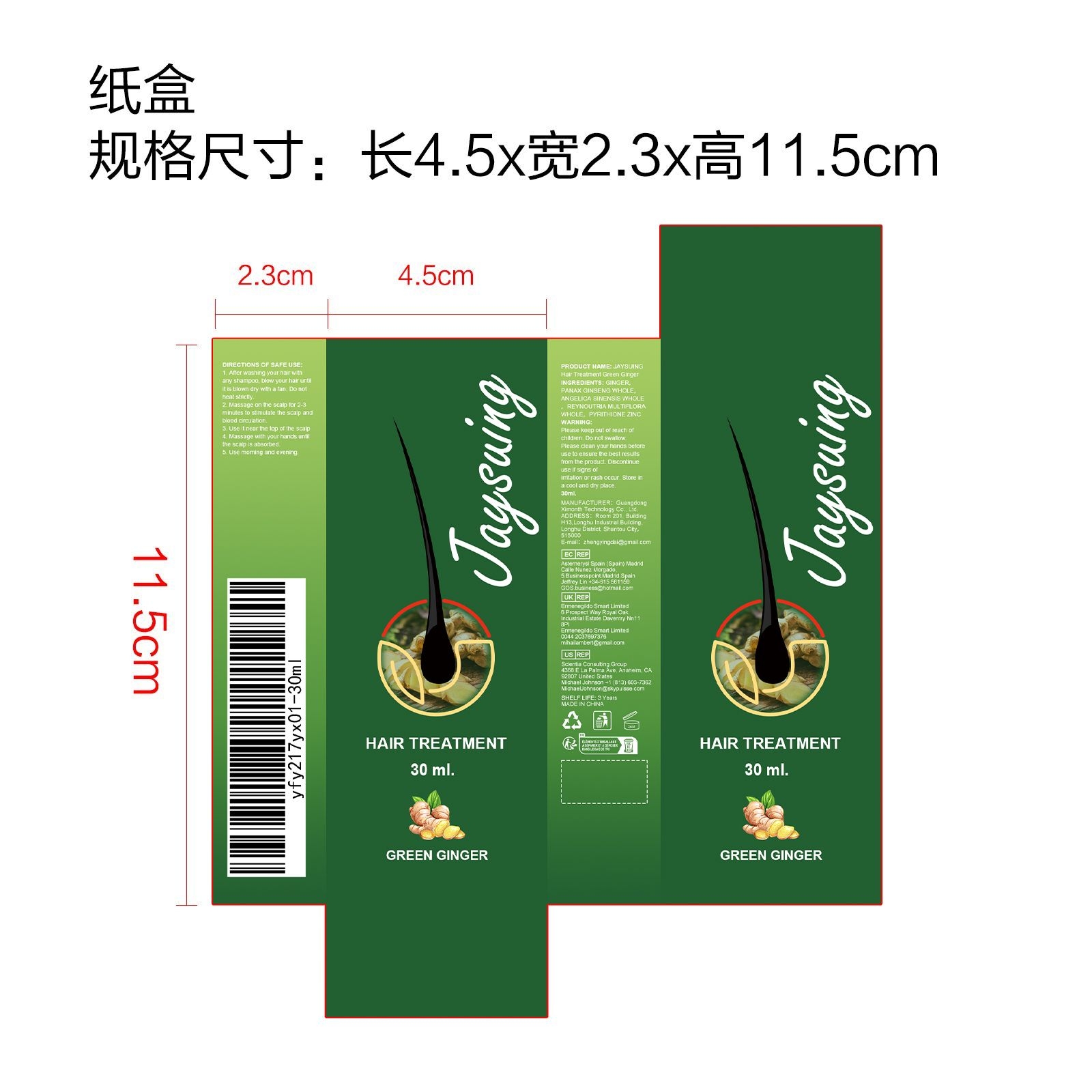 DRUG LABEL: JAYSUING Hair Treatment Green Ginger
NDC: 84660-038 | Form: LIQUID
Manufacturer: Guangdong Ximonth Technology Co., Ltd.
Category: otc | Type: HUMAN OTC DRUG LABEL
Date: 20241006

ACTIVE INGREDIENTS: GINGER 7.5 mg/30 mg; REYNOUTRIA MULTIFLORA WHOLE 3 mg/30 mg; ANGELICA SINENSIS WHOLE 6 mg/30 mg; PANAX GINSENG WHOLE 4.5 mg/30 mg
INACTIVE INGREDIENTS: PYRITHIONE ZINC 9 mg/30 mg

Active Ingredient(s)

GINGER，PANAX GINSENG WHOLE，ANGELICA SINENSIS WHOLE，REYNOUTRIA MULTIFLORA WHOLE

Purpose

Promotes hair growth

Do not use

Discontinue use if signs of irritation or rash occur.

STOP USE

Discontinue use if signs of irritation or rash occur.

KEEP OUT OF REACH OF CHILDREN

Please keep out of reach of children. Do not swallow.

Warnings

Please keep out of reach of children.Do not swallow.Please clean your hands before use to ensure the best results from the product.Discontinue use if signs of irritation or rash occur.Store in a cool and dry place.

STORAGE AND HANDLING

Avoid freezing and excessive heat above 40C (104F) ）
Store in a cool and dry place.

Use

1. After washing your hair with any shampoo, blow your hair until it is blown dry with a fan. Do not heat strictly.
2. Massage on the scalp for 2-3 minutes to stimulate the scalp and blood circulation.
3. Use it near the top of the scalp.
4. Massage with your hands until the scalp is absorbed.
5. Use morning and evening.

INACTIVE INGREDIENT

PYRITHIONE ZINC